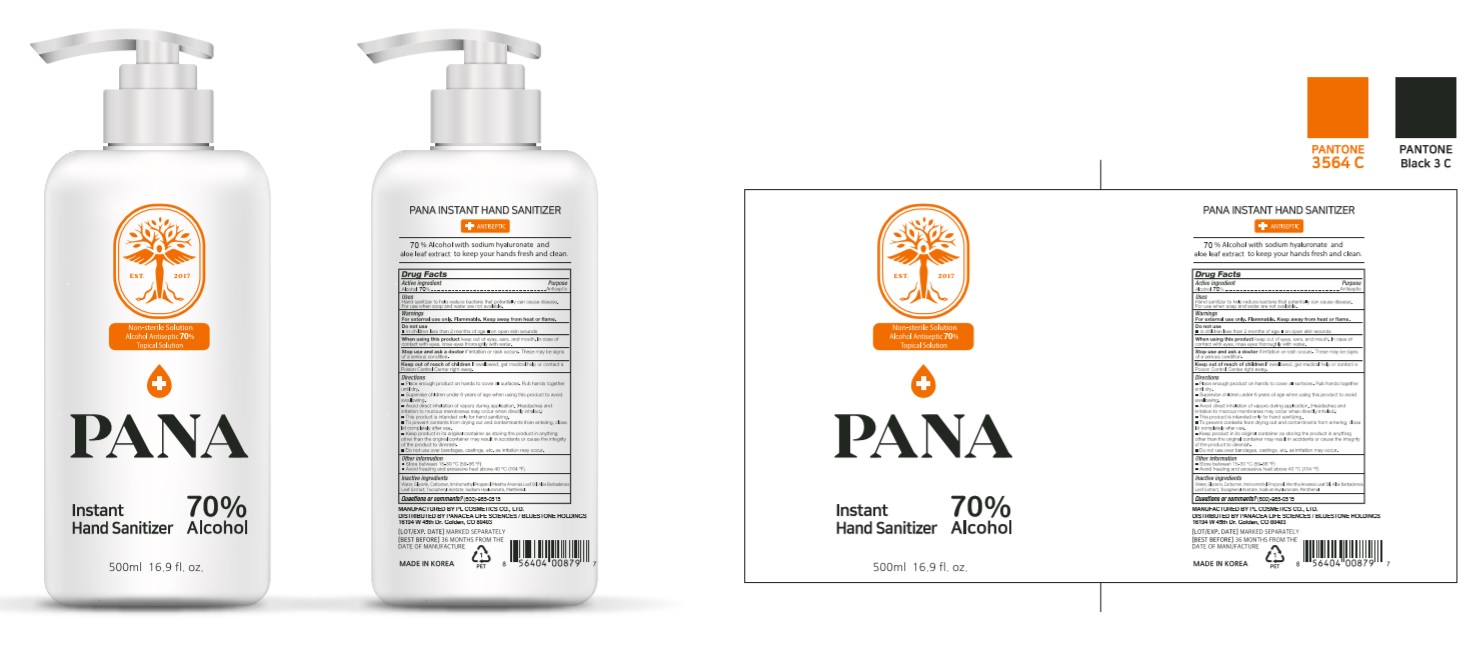 DRUG LABEL: 70% Pana Instant Hand Sanitizer
NDC: 74339-7570 | Form: GEL
Manufacturer: PL COSMETIC
Category: otc | Type: HUMAN OTC DRUG LABEL
Date: 20200428

ACTIVE INGREDIENTS: ALCOHOL 350 mL/500 mL
INACTIVE INGREDIENTS: PANTHENOL; MENTHA ARVENSIS LEAF OIL; GLYCERIN; .ALPHA.-TOCOPHEROL ACETATE; ALOE VERA LEAF; WATER; AMINOMETHYL PROPANEDIOL; CARBOMER HOMOPOLYMER, UNSPECIFIED TYPE; HYALURONATE SODIUM

70% Pana Instant Hand Sanitizer 74339-7570-1